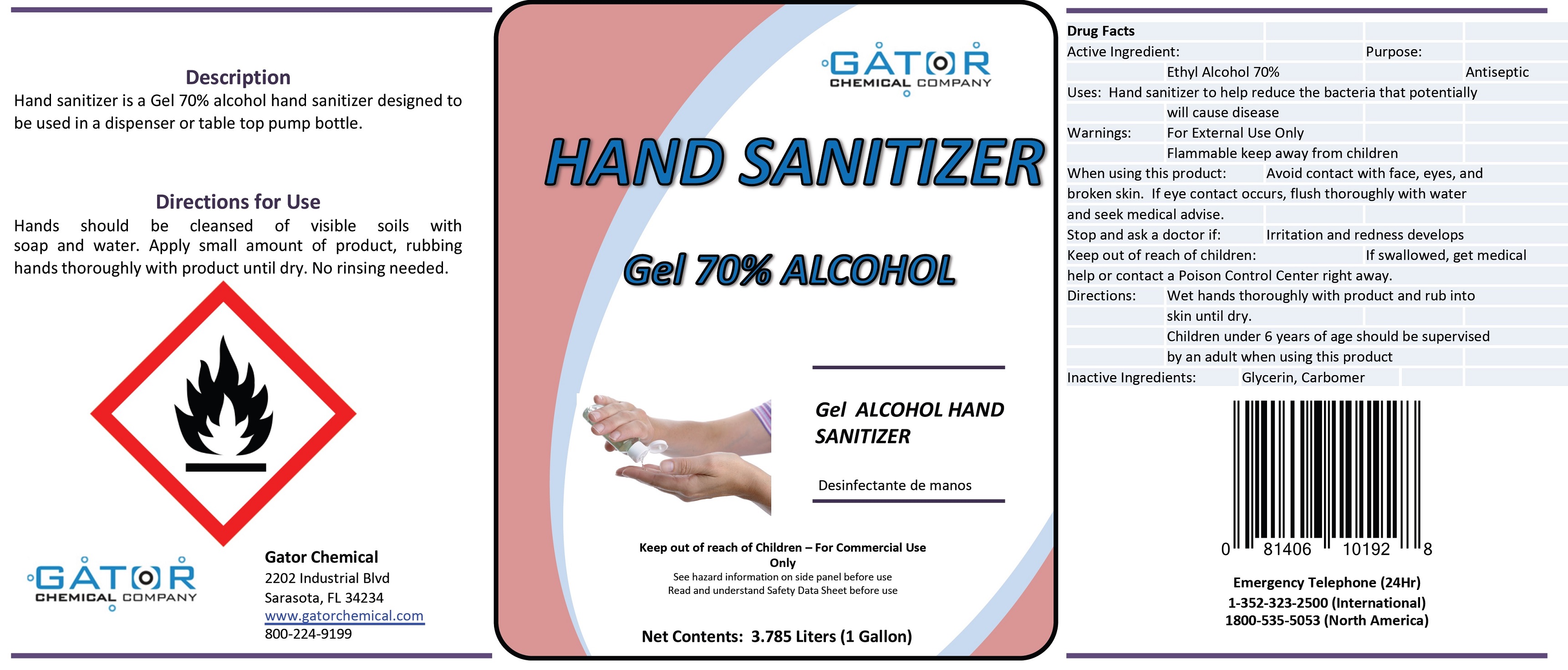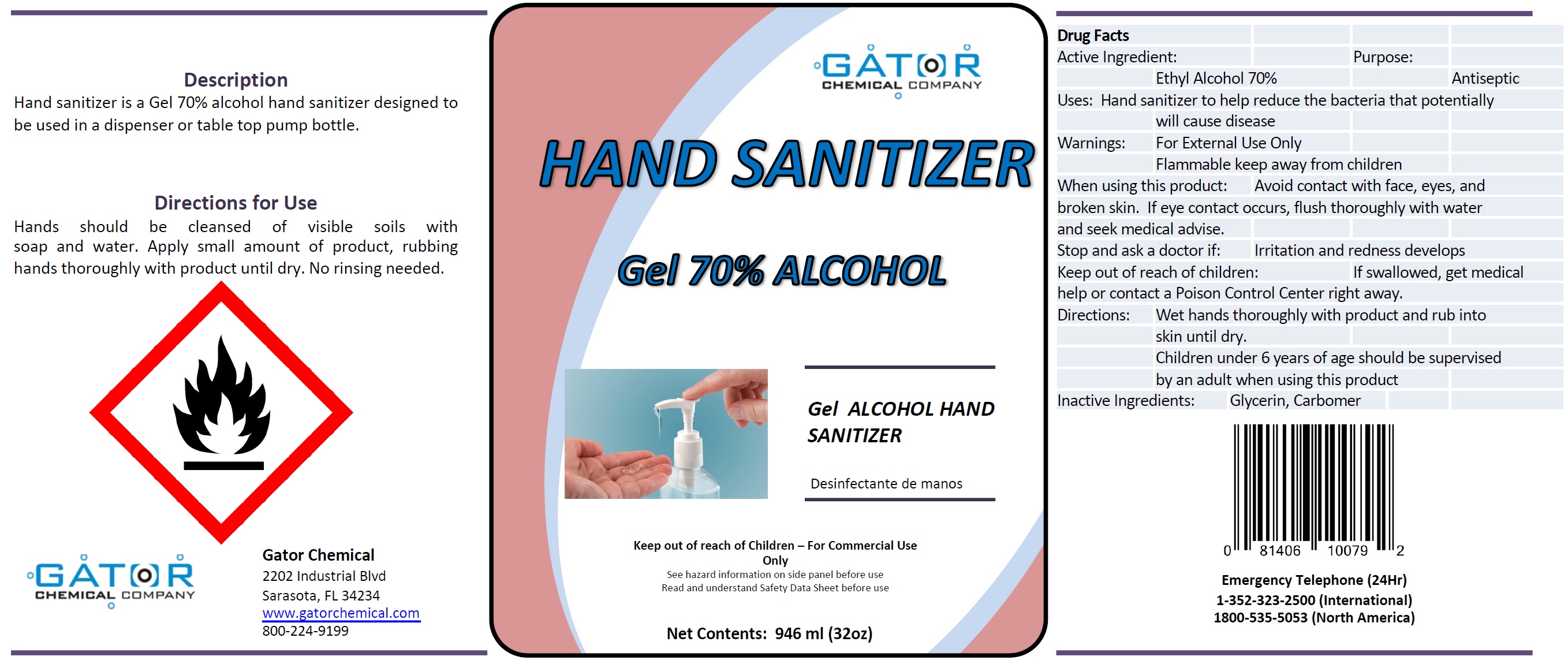 DRUG LABEL: Hand Sanitizer Gel
NDC: 77188-002 | Form: GEL
Manufacturer: Resource One Inc
Category: otc | Type: HUMAN OTC DRUG LABEL
Date: 20201104

ACTIVE INGREDIENTS: ALCOHOL 0.7 mL/1 mL
INACTIVE INGREDIENTS: GLYCERIN; CARBOMER HOMOPOLYMER, UNSPECIFIED TYPE

Hand Sanitizer Gel

Active Ingredient:

Ethyl Alcohol 70%

Purpose:

Antiseptic

Uses:

Hand sanitizer to help reduce the bacteria that potentially will cause disease

Warnings:

For External Use Only
Flammable keep away from children

When using this product:

Avoid contact with face, eyes, and broken skin. If eye contact occurs, flush thoroughly with water and seek medical advise.

Stop and ask a doctor if:

Irritation and redness develops

Keep out of reach of children:

If swallowed, get medical help or contact a Poison Control Center right away.

Directions:

Wet hands thoroughly with product and rub into skin until dry.
Children under 6 years of age should be supervised by an adult when using this product

Inactive Ingredients:

Glycerin, Carbomer